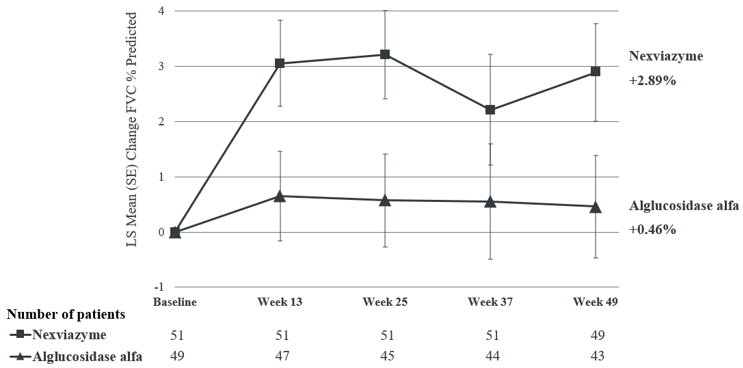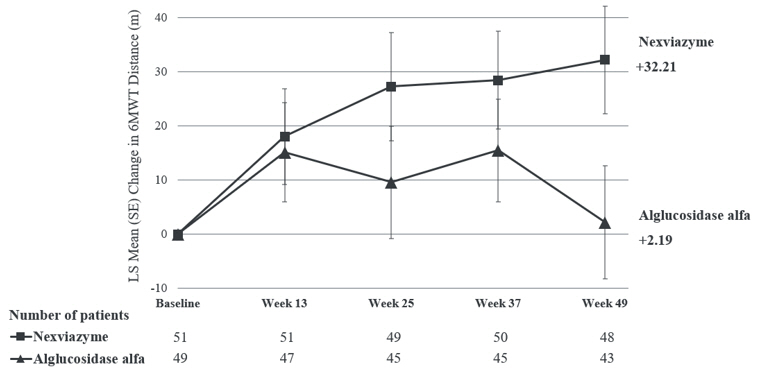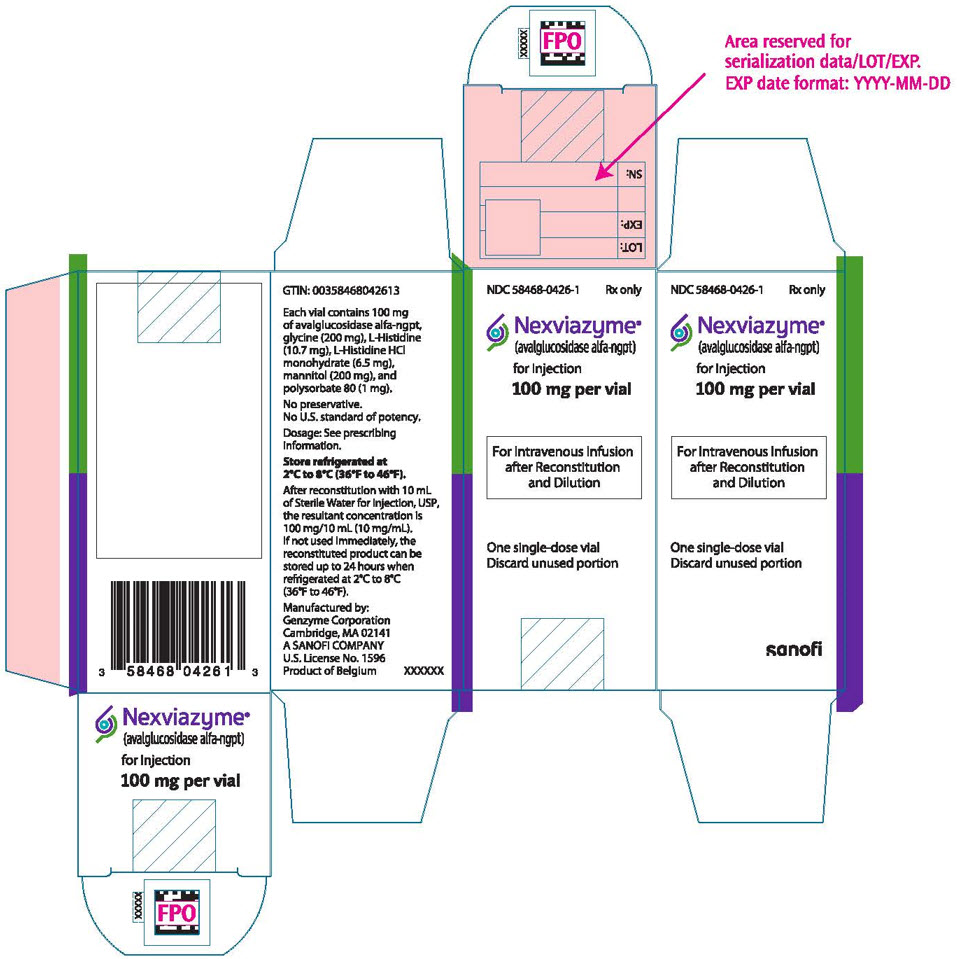 DRUG LABEL: Nexviazyme
NDC: 58468-0426 | Form: INJECTION, POWDER, LYOPHILIZED, FOR SOLUTION
Manufacturer: Genzyme Corporation
Category: prescription | Type: HUMAN PRESCRIPTION DRUG LABEL
Date: 20250605

ACTIVE INGREDIENTS: AVALGLUCOSIDASE ALFA 100 mg/10 mL
INACTIVE INGREDIENTS: GLYCINE 200 mg/10 mL; HISTIDINE 10.7 mg/10 mL; HISTIDINE MONOHYDROCHLORIDE MONOHYDRATE 6.5 mg/10 mL; MANNITOL 200 mg/10 mL; POLYSORBATE 80 1 mg/10 mL

HIGHLIGHTS OF PRESCRIBING INFORMATION

These highlights do not include all the information needed to use NEXVIAZYME® safely and effectively. See full prescribing information for NEXVIAZYME.
NEXVIAZYME (avalglucosidase alfa-ngpt) for injection, for intravenous use
Initial U.S. Approval: 2021

WARNING: SEVERE HYPERSENSITIVITY REACTIONS, INFUSION-ASSOCIATED REACTIONS, and RISK OF ACUTE CARDIORESPIRATORY FAILURE IN SUSCEPTIBLE PATIENTS

See full prescribing information for complete boxed warning.

Hypersensitivity Reactions Including Anaphylaxis

- Appropriate medical monitoring and support measures, including cardiopulmonary resuscitation equipment, should be readily available. If a severe hypersensitivity reaction occurs, discontinue NEXVIAZYME immediately and initiate appropriate medical treatment. (5.1)

Infusion-Associated Reactions (IARs)

- If severe IARs occur, consider immediate discontinuation and initiation of appropriate medical treatment. (5.2)

Risk of Acute Cardiorespiratory Failure in Susceptible Patients

- Patients susceptible to fluid volume overload, or those with acute underlying respiratory illness or compromised cardiac or respiratory function, may be at risk of serious exacerbation of their cardiac or respiratory status during NEXVIAZYME infusion. (5.3)

RECENT MAJOR CHANGES

Dosage and Administration (2.1, 2.2) | 9/2023
Warnings and Precautions (5.1, 5.2) | 9/2023

1 INDICATIONS AND USAGE

NEXVIAZYME is a hydrolytic lysosomal glycogen-specific enzyme indicated for the treatment of patients 1 year of age and older with late-onset Pompe disease (lysosomal acid alpha-glucosidase [GAA] deficiency). (1)

2 DOSAGE AND ADMINISTRATION

- Consider administering antihistamines, antipyretics, and/or corticosteroids prior to NEXVIAZYME administration to reduce the risk of IARs. (2.1)
- NEXVIAZYME is administered as intravenous infusion. For patients weighing (2.2):
  - ≥30 kg, the recommended dosage is 20 mg/kg (of actual body weight) every two weeks.
  - <30 kg, the recommended dosage is 40 mg/kg (of actual body weight) every two weeks.
- See the full prescribing information for dosage modifications due to hypersensitivity reactions or IARs. (2.3)
- Must be reconstituted and diluted prior to use. (2.4)
- For instructions on storage and administration, see full prescribing information. (2.5, 2.6)

3 DOSAGE FORMS AND STRENGTHS

For injection: 100 mg of avalglucosidase alfa-ngpt as a lyophilized powder in a single-dose vial for reconstitution. (3)

4 CONTRAINDICATIONS

None. (4)

5 WARNINGS AND PRECAUTIONS

See boxed warning. (5.1, 5.2, 5.3)

6 ADVERSE REACTIONS

The most common adverse reactions (>5%) were headache, fatigue, diarrhea, nausea, arthralgia, dizziness, myalgia, pruritus, vomiting, dyspnea, erythema, paresthesia and urticaria. (6.1)

To report SUSPECTED ADVERSE REACTIONS, contact Genzyme at 1-800-633-1610, option 1 or FDA at 1-800-FDA-1088 or www.fda.gov/medwatch.

FULL PRESCRIBING INFORMATION

WARNING: SEVERE HYPERSENSITIVITY REACTIONS, INFUSION-ASSOCIATED REACTIONS, and RISK OF ACUTE CARDIORESPIRATORY FAILURE IN SUSCEPTIBLE PATIENTS

Hypersensitivity Reactions Including Anaphylaxis

Patients treated with NEXVIAZYME have experienced life-threatening hypersensitivity reactions, including anaphylaxis. Appropriate medical monitoring and support measures, including cardiopulmonary resuscitation equipment, should be readily available during NEXVIAZYME administration. If a severe hypersensitivity reaction (e.g., anaphylaxis) occurs, discontinue NEXVIAZYME immediately and initiate appropriate medical treatment. In patients with severe hypersensitivity reactions, a desensitization procedure to NEXVIAZYME may be considered [see Warnings and Precautions (5.1)].

Infusion-Associated Reactions (IARs)

Patients treated with NEXVIAZYME have experienced severe IARs. If severe IARs occur, consider immediate discontinuation of NEXVIAZYME, initiation of appropriate medical treatment, and the benefits and risks of readministering NEXVIAZYME following severe IARs. Patients with an acute underlying illness at the time of NEXVIAZYME infusion may be at greater risk for IARs. Patients with advanced Pompe disease may have compromised cardiac and respiratory function, which may predispose them to a higher risk of severe complications from IARs [see Warnings and Precautions (5.2)].

Risk of Acute Cardiorespiratory Failure in Susceptible Patients

Patients susceptible to fluid volume overload, or those with acute underlying respiratory illness or compromised cardiac or respiratory function for whom fluid restriction is indicated may be at risk of serious exacerbation of their cardiac or respiratory status during NEXVIAZYME infusion. More frequent monitoring of vitals should be performed during NEXVIAZYME infusion in such patients [see Warnings and Precautions (5.3)].

1 INDICATIONS AND USAGE

NEXVIAZYME is indicated for the treatment of patients 1 year of age and older with late-onset Pompe disease (lysosomal acid alpha-glucosidase [GAA] deficiency).

2 DOSAGE AND ADMINISTRATION

2.1 Recommendations Prior to NEXVIAZYME Treatment

- Prior to NEXVIAZYME administration, consider pretreating with antihistamines, antipyretics, and/or corticosteroids [see Warnings and Precautions (5.1, 5.2)].
- NEXVIAZYME must be reconstituted and diluted prior to use [see Dosage and Administration (2.4)].
- Appropriate medical monitoring and support measures, including cardiopulmonary resuscitation equipment, should be readily available during NEXVIAZYME administration.

2.2 Recommended Dosage and Administration

- NEXVIAZYME is administered as intravenous infusion. For patients weighing:
  - 30 kg or more- the recommended dosage is 20 mg/kg (of actual body weight) every two weeks [see Dosage and Administration (2.6)]
  - Less than 30 kg- the recommended dosage is 40 mg/kg (of actual body weight) every two weeks [see Dosage and Administration (2.6)]
- The initial recommended infusion rate is 1 mg/kg/hour. Gradually increase the infusion rate every 30 minutes if there are no signs of infusion-associated reactions (IARs) [see Dosage and Administration (2.6)]. If one or more doses are missed, restart NEXVIAZYME treatment as soon as possible, maintaining the 2 week interval between infusions thereafter.

2.3 Administration Modifications Due to Hypersensitivity Reactions and/or Infusion-Associated Reactions

- In the event of a severe hypersensitivity reaction (e.g., anaphylaxis) or severe infusion-associated reaction (IAR), immediately discontinue NEXVIAZYME administration and initiate appropriate medical treatment. For additional recommendations in the event of a severe hypersensitivity reaction or IAR, [see Warnings and Precautions (5.1, 5.2)].
- In the event of a mild to moderate hypersensitivity reaction or a mild to moderate IAR, consider temporarily holding the infusion for 30 minutes or slowing the infusion rate by 50% [see Dosage and Administration (2.6)] and initiating appropriate medical treatment [see Warnings and Precautions (5.1, 5.2)].
  - If symptoms persist for longer than 30 minutes despite holding or slowing the infusion, stop the infusion and monitor the patient. Consider re-initiating the infusion on the same day when symptoms subside at 50% of the rate at which the reaction occurred with appropriate pretreatment.
  - If symptoms subside after holding the infusion, resume infusion at 50% of the rate at which the reaction occurred, and subsequently increase the infusion rate every 15 to 30 minutes by 50% as tolerated. Alternatively, if symptoms subside after slowing the infusion, complete the infusion at the reduced rate as tolerated.
  - Starting with the next infusion, increase the infusion rate until the infusion rate at which the reaction occurred is reached. Consider continuing to increase the infusion rate in a stepwise manner until reaching the recommended infusion rate. Closely monitor the patient.

2.4 Reconstitution and Dilution Instructions

Reconstitute and dilute NEXVIAZYME in the following manner. Use aseptic technique during preparation.

Reconstitute the Lyophilized Powder

1. Determine the number of NEXVIAZYME vials to be reconstituted based on actual body weight in kg and the recommended dose [see Dosage and Administration (2.2)]. Round the number of vials up to the next whole number.
2. Remove the required number of NEXVIAZYME vials from the refrigerator and allow the vials to sit for 30 minutes at room temperature 20°C to 25°C (68°F to 77°F) before use.
3. Reconstitute each vial by injecting 10 mL of Sterile Water for Injection, down the inside wall of each vial. Avoid adding the Sterile Water for Injection to the vial forcefully or directly onto the lyophilized powder to minimize foaming.
4. Gently tilt and roll each vial to enhance the dissolution process. Do not invert, swirl, or shake the vial. Allow the solution to become dissolved. Each vial will yield a concentration of 100 mg/10 mL (10 mg/mL) of avalglucosidase alfa-ngpt.
5. Visually inspect the reconstituted solution in the vials for particulate matter and discoloration. The reconstituted solution should be clear, colorless to pale-yellow. Discard if particles are present or the solution is discolored.

Dilute the Reconstituted Solution

1. Select an appropriate size 5% Dextrose Injection infusion bag and prepare by removing a volume equal to the required NEXVIAZYME volume and any overfill to achieve a fixed total volume per Table 1 based on actual body weight.
2. Slowly withdraw the required volume of reconstituted solution from the NEXVIAZYME vial(s). Discard any unused reconstituted solution remaining in the vial.
3. Gently inject the NEXVIAZYME reconstituted solution into the port of the 5% Dextrose Injection bag. Avoid foaming or agitation of the infusion bag and avoid introducing air into the infusion bag.
4. Gently invert the infusion bag to mix the solution. Do not shake. After dilution, the solution will have a final concentration of 0.5 to 4 mg/mL of avalglucosidase alfa-ngpt.

Administer the diluted solution without delay. The recommended infusion duration is between 4 to 7 hours [see Dosage and Administration (2.6)]. Discard any unused diluted solution after 9 hours.

Table 1: Projected Intravenous Infusion Volume for NEXVIAZYME Administration According to Actual Body Weight
Patient Actual Body Weight Range (kg) | Total Infusion Volume (mL) for 20 mg/kg | Total Infusion Volume (mL) for 40 mg/kg
5 to 9.9 kg | N/A | 100 mL
10 to 19.9 kg | N/A | 200 mL
20 to 29.9 kg | N/A | 300 mL
30 to 34.9 kg | 200 mL | N/A
35 to 49.9 kg | 250 mL | N/A
50 to 59.9 kg | 300 mL | N/A
60 to 99.9 kg | 500 mL | N/A
100 to 119.9 kg | 600 mL | N/A
120 to 140 kg | 700 mL | N/A

2.5 Storage Instructions for the Reconstituted and Diluted Product

Storage of the Reconstituted Solution

- Dilute the reconstituted solution without delay. If the reconstituted solution is not diluted immediately, refrigerate at 2°C to 8°C (36°F to 46°F) for up to 24 hours.
- Do not freeze.

Storage of the Diluted Solution

- If the diluted solution is not used immediately, refrigerate the diluted solution at 2°C to 8°C (36°F to 46°F) for up to 24 hours.
- The diluted solution must be infused within 9 hours after removal from the refrigerator, inclusive of infusion time, or discarded.
- Once the diluted solution is removed from the refrigerator, it must not be restored back into the refrigerator.
- Do not freeze.

2.6 Administration Instructions

1. If the diluted solution was refrigerated, allow solution to equilibrate to room temperature for 30 minutes prior to infusion.
2. It is recommended to use an in-line, low protein-binding, 0.2 micron filter during administration.
3. Administer the infusion incrementally, as determined by the patient's response and comfort.
  When the recommended dose is 20 mg/kg
  - Initial and Subsequent Infusions: The initial recommended infusion rate is 1 mg/kg/hour (see Table 2). If there are no signs of hypersensitivity or infusion-associated reactions (IARs), gradually increase the infusion rate every 30 minutes in each of the following three steps: 3 mg/kg/hour, 5 mg/kg/hour, and then 7 mg/kg/hour; then, maintain the infusion rate at 7 mg/kg/hour until the infusion is complete. The approximate total infusion duration is 4 to 5 hours.
  Table 2: Recommended Infusion Rates at 20 mg/kg Dose
  Dose | Step 1 | Step 2 | Step 3 | Step 4 | Step 5
  20 mg/kg | 1 mg/kg/hour | 3 mg/kg/hour | 5 mg/kg/hour | 7 mg/kg/hour | Continue 7 mg/kg/hour
  Start infusion at step 1 and in absence of infusion-associated reaction increase infusion rate sequentially per the steps of infusion every 30 minutes until completion (total time approximately 4 to 5 hours).
  When the recommended dose is 40 mg/kg
  - Initial Infusion: The initial recommended infusion rate is 1 mg/kg/hour (see Table 3). If there are no signs of hypersensitivity or IARs, gradually increase the infusion rate every 30 minutes in each of the following three steps: 3 mg/kg/hour, 5 mg/kg/hour, and then 7 mg/kg/hour; then, maintain the infusion rate at 7 mg/kg/hour until the infusion is complete (4-step process). The approximate total infusion duration is 7 hours.
  - Subsequent Infusions: The initial recommended infusion rate is 1 mg/kg/hour (see Table 3) with gradual increase in infusion rate every 30 minutes if there are no signs of hypersensitivity or IARs. The process may use either the above 4-step process or the following 5-step process: 3 mg/kg/hour, 6 mg/kg/hour, 8 mg/kg/hour, and then 10 mg/kg/hour; then, maintain the infusion rate at 10 mg/kg/hour until the infusion is complete. The approximate total 5-step infusion duration is 5 hours.
  Table 3: Recommended Infusion Rates at 40 mg/kg Dose
  Dose |  | Step 1 | Step 2 | Step 3 | Step 4 | Step 5
  40 mg/kg | Initial infusion rate | 1 mg/kg/hour | 3 mg/kg/hour | 5 mg/kg/hour | 7 mg/kg/hour | Continue 7 mg/kg/hour
  40 mg/kg | Subsequent infusions (optional) | 1 mg/kg/hour | 3 mg/kg/hour | 6 mg/kg/hour | 8 mg/kg/hour | Continue 10 mg/kg/hour
  Start infusion at step 1 and in absence of infusion-associated reaction increase infusion rate sequentially per the steps of infusion every 30 minutes until completion. Total time for initial infusion approximately 7 hours and can optionally increase rate of subsequent infusions to decrease total duration to 5 hours.
4. After the infusion is complete, flush the intravenous line with 5% Dextrose Injection.
5. Do not infuse NEXVIAZYME in the same intravenous line with other products.

3 DOSAGE FORMS AND STRENGTHS

For injection: 100 mg of avalglucosidase alfa-ngpt as a white to pale-yellow lyophilized powder in a single-dose vial for reconstitution.

4 CONTRAINDICATIONS

None.

5 WARNINGS AND PRECAUTIONS

5.1 Hypersensitivity Reactions Including Anaphylaxis

Life-threatening hypersensitivity reactions, including anaphylaxis, have been reported in NEXVIAZYME-treated patients. In NEXVIAZYME clinical studies, 67 (48%) NEXVIAZYME-treated patients experienced hypersensitivity reactions, including 6 (4%) patients who reported severe hypersensitivity reactions and 3 (2%) patients who experienced anaphylaxis; 2 (1%) patients who experienced anaphylaxis discontinued from the study. Some of the hypersensitivity reactions were IgE mediated. Symptoms of severe hypersensitivity reactions (e.g., anaphylaxis) included chest discomfort, erythema, generalized edema, hypotension, hypoxia, rash, respiratory distress, tongue edema, and urticaria.

Prior to NEXVIAZYME administration, consider pretreating with antihistamines, antipyretics, and/or corticosteroids. Appropriate medical monitoring and support measures, including cardiopulmonary resuscitation equipment, should be readily available during NEXVIAZYME administration.

- If a severe hypersensitivity reaction (e.g., anaphylaxis) occurs, discontinue NEXVIAZYME immediately and initiate appropriate medical treatment. Consider the risks and benefits of re-administering NEXVIAZYME following severe hypersensitivity reactions (including anaphylaxis). Patients may be rechallenged using slower infusion rates at a dosage lower than the recommended dosage. In patients with severe hypersensitivity reaction, desensitization measures to NEXVIAZYME may be considered. If the decision is made to readminister NEXVIAZYME, ensure the patient tolerates the infusion. Once the patient tolerates the infusion, the dosage (dose and/or the rate) may be increased to reach the recommended dosage.
- If a mild or moderate hypersensitivity reaction occurs, consider temporarily holding the infusion or slowing the infusion rate [see Dosage and Administration (2.3)].

5.2 Infusion-Associated Reactions

In clinical studies, IARs were reported to occur at any time during and/or within a few hours after the NEXVIAZYME infusion and were more likely to occur with higher infusion rates. IARs were reported in 48 (34%) NEXVIAZYME-treated patients in all clinical studies. In these studies, 5 (4%) NEXVIAZYME-treated patients reported 10 severe IARs including symptoms of chest discomfort, decreased or increased blood pressure, dysphagia, erythema, generalized edema, hypoxia, nausea, respiratory distress, tongue edema, and urticaria. The majority of IARs were assessed as mild to moderate. IARs that led to treatment discontinuation were chest discomfort, cough, dizziness, erythema, flushing, nausea, ocular hyperemia, respiratory distress, and urticaria. Increased incidence of IARs was observed in patients with higher ADA titers [see Adverse Reactions (6.1)].

Prior to NEXVIAZYME administration, consider pretreating with antihistamines, antipyretics, and/or corticosteroids to reduce the risk of IARs. However, IARs may still occur in patients after receiving pretreatment.

If a severe IAR occurs, discontinue NEXVIAZYME immediately and initiate appropriate medical treatment. Consider the benefits and risks of readministering NEXVIAZYME following a severe IAR. Patients may be rechallenged using slower infusion rates at a dosage lower than the recommended dosage. Once the patient tolerates the infusion, the dosage (dose and/or the rate) may be increased to reach the recommended dosage.

If a mild or moderate IAR occurs, consider temporarily holding the infusion or slowing the infusion rate [see Dosage and Administration (2.3)].

Patients with an acute underlying illness at the time of NEXVIAZYME infusion appear to be at greater risk for IARs. Patients with advanced Pompe disease may have compromised cardiac and respiratory function, which may predispose them to a higher risk of severe complications from IARs.

5.3 Risk of Acute Cardiorespiratory Failure in Susceptible Patients

Patients susceptible to fluid volume overload, or those with acute underlying respiratory illness or compromised cardiac or respiratory function for whom fluid restriction is indicated may be at risk of serious exacerbation of their cardiac or respiratory status during the NEXVIAZYME infusion. More frequent monitoring of vitals should be performed during NEXVIAZYME infusion in these patients. Some patients may require prolonged observation times.

6 ADVERSE REACTIONS

The following serious adverse reactions are discussed in greater detail in other sections of the labeling:

- Hypersensitivity Reactions Including Anaphylaxis [see Warnings and Precautions (5.1)]
- Infusion-Associated Reactions (IARs) [see Warnings and Precautions (5.2)]

6.1 Clinical Trials Experience

Because clinical trials are conducted under widely varying conditions, adverse reaction rates observed in the clinical trials of a drug cannot be directly compared to rates in the clinical trials of another drug and may not reflect the rates observed in practice.

Adverse Reactions from Clinical Trials in the Pompe Disease Population

The pooled safety analysis from 4 clinical trials in the Pompe disease population (including Study 1) with a mean exposure of 26 months and up to 85 months of treatment included a total of 141 NEXVIAZYME-treated patients (118 adult and 23 pediatric patients [see Clinical Studies (14.1)].

Adverse reactions were similar across both adult and pediatric populations.

Serious adverse reactions reported in 2 or more NEXVIAZYME-treated patients were respiratory distress, chills, and pyrexia.

A total of 4 NEXVIAZYME-treated patients in clinical trials permanently discontinued NEXVIAZYME due to adverse reactions, including 3 patients who discontinued the treatment because of a serious adverse reaction.

The most frequently reported adverse reactions (>5%) in the pooled safety population were abdominal pain, arthralgia, chills, diarrhea, dizziness, dyspnea, erythema, fatigue, flushing, headache, hypertension, hypotension, myalgia, nausea, pruritus, pyrexia, rash, vomiting, and urticaria.

Hypersensitivity reactions were reported in 67 (48%) NEXVIAZYME-treated patients, including 6 (4%) patients who reported severe hypersensitivity reactions. Symptoms of severe hypersensitivity reactions (e.g., anaphylaxis) included chest discomfort, erythema, generalized edema, hypotension, hypoxia, rash, respiratory distress, tongue edema, and urticaria.

IARs were reported in 48 (34%) NEXVIAZYME-treated patients. Six (4%) NEXVIAZYME-treated patients reported 13 severe IARs including symptoms of chest discomfort, decreased or increased blood pressure, dysphagia, erythema, generalized edema, hypoxia, nausea, respiratory distress, tongue edema, and urticaria. IARs reported in more than 1 patient included chest discomfort, cyanosis, decreased or increased blood pressure, diarrhea, dizziness, erythema, fatigue, feeling hot or cold, generalized edema, headache, hyperhidrosis, hypoxia, influenza-like illness, nausea, pain, pruritus, pyrexia, rash, respiratory distress, tachycardia, throat irritation, tongue edema, tremor, urticaria, and vomiting.

Adverse Reactions from Clinical Trials in Late-Onset Pompe Disease (LOPD)

In Study 1, 100 patients aged 16 to 78 years of age with LOPD (naïve to enzyme replacement therapy) were treated with either 20 mg/kg of NEXVIAZYME (n=51) or 20 mg/kg of alglucosidase alfa (n=49) given every other week as an intravenous infusion for 49 weeks followed by an open-label extension period [see Clinical Studies (14.1)].

During the double-blind active-controlled period of 49 weeks, serious adverse reactions were reported in 1 (2%) patient treated with NEXVIAZYME and in 3 (6%) patients treated with alglucosidase alfa. The most frequently reported adverse reactions in (>5%) NEXVIAZYME-treated patients were headache, fatigue, diarrhea, nausea, arthralgia, dizziness, myalgia, pruritus, vomiting, dyspnea, erythema, paresthesia, and urticaria.

IARs were reported in 13 (25%) of the NEXVIAZYME-treated patients. IARs reported in more than 1 patient on NEXVIAZYME were mild to moderate and included headache, diarrhea, pruritus, urticaria, and rash. None of them were severe IARs. IARs were reported in 16 (33%) patients treated with alglucosidase alfa. IARs reported in more than 1 patient on alglucosidase alfa were mild to severe and included dizziness, flushing, dyspnea, nausea, pruritis, rash, erythema, chills, and feeling hot. Severe IARs were reported in 2 patients treated with alglucosidase alfa.

Table 4 summarizes the adverse reactions that occurred in at least 3 NEXVIAZYME-treated patients (≥6%) in Study 1. Study 1 was not designed to demonstrate a statistically significant difference in the incidence of adverse reactions in the NEXVIAZYME and the alglucosidase alfa treatment groups.

Table 4: Adverse Reactions Reported in at Least 6% of NEXVIAZYME-Treated Patients with LOPD in Study 1
Adverse Reaction | NEXVIAZYME (N=51) n (%) | Alglucosidase Alfa (N=49) n (%)
Headache | 11 (22%) | 16 (33%)
Fatigue | 9 (18%) | 7 (14%)
Diarrhea | 6 (12%) | 8 (16%)
Nausea | 6 (12%) | 7 (14%)
Arthralgia | 5 (10%) | 8 (16%)
Dizziness | 5 (10%) | 4 (8%)
Myalgia | 5 (10%) | 7 (14%)
Pruritus | 4 (8%) | 4 (8%)
Vomiting | 4 (8%) | 3 (6%)
Dyspnea | 3 (6%) | 4 (8%)
Erythema | 3 (6%) | 3 (6%)
Paresthesia | 3 (6%) | 2 (4%)
Urticaria | 3 (6%) | 1 (2%)

Immunogenicity: Anti-Drug Antibody-Associated Adverse Reactions

In enzyme replacement therapy (ERT)-naïve NEXVIAZYME-treated patients (mean of 47 months, up to 100 months of treatment), the incidence of [see Warnings and Precautions (5.2) and Clinical Pharmacology (12.6)] IARs was 69% (9/13) in patients with an anti-drug antibody (ADA) peak titer ≥12,800, compared with incidences of 27% (12/44) in those with ADA peak titer <12,800 and 33% (1/3) in those who were ADA-negative.

In ERT-experienced adult patients, the incidence of IARs and hypersensitivity reactions were higher in patients who developed ADA compared to patients who were ADA-negative [see Clinical Pharmacology (12.6)].

In adults, one ERT-naïve patient (ADA peak titer 3,200) and 2 ERT-experienced patients (peak ADA titers; 800 and 12,800, respectively) developed anaphylaxis. One ERT-experienced pediatric patient (peak ADA titer 6,400) developed anaphylaxis [see Warnings and Precautions (5.1)].

8 USE IN SPECIFIC POPULATIONS

8.1 Pregnancy

Risk Summary

Available data from case reports of NEXVIAZYME use in pregnant women are insufficient to evaluate for a drug associated risk of major birth defects, miscarriage, or adverse maternal or fetal outcomes. However, available data from postmarketing reports and published case reports on alglucosidase alfa (another hydrolytic lysosomal glycogen-specific enzyme replacement therapy) use in pregnant women have not identified a drug-associated risk of adverse pregnancy outcomes. The continuation of treatment for Pompe disease during pregnancy should be individualized to the pregnant woman. Untreated Pompe disease may result in worsening disease symptoms in pregnant women (see Clinical Considerations).

Embryo-fetal toxicity studies performed in pregnant mice resulted in maternal toxicity related to an immunologic response (including an anaphylactoid response) and embryo-fetal loss at 17 times the human steady-state AUC at the recommended biweekly dose of 20 mg/kg for LOPD patients weighing ≥30 kg or 10 times the human steady-state AUC at the recommended biweekly dose of 40 mg/kg for LOPD patients weighing <30 kg. Avalglucosidase alfa-ngpt did not cross the placenta in mice, therefore, the adverse effects were likely related to the immunologic response in the mothers. Embryo-fetal toxicity studies performed in pregnant rabbits showed no adverse effects on the fetuses at exposure up to 91 times the human steady-state AUC at the recommended biweekly dosage of 20 mg/kg for LOPD patients weighing ≥30 kg or 50 times the human steady-state AUC at the recommended biweekly dose of 40 mg/kg for LOPD patients weighing <30 kg (see Data).

The background risk of major birth defects and miscarriage for the indicated population is unknown. All pregnancies have a background risk of birth defect, miscarriage, or other adverse outcomes. In the U.S. general population, the background risk of major birth defects and miscarriage in clinically recognized pregnancies is 2% to 4% and 15% to 20%, respectively.

Pregnant women exposed to NEXVIAZYME, or their healthcare providers, should report NEXVIAZYME exposure by calling 1-800-633-1610, option 1.

Clinical Considerations

Disease-associated maternal and/or embryo-fetal risk

Untreated Pompe disease has been associated with worsening respiratory and musculoskeletal symptoms in some pregnant women.

Data

Animal data

The majority of reproductive toxicity studies in mice included the pretreatment with diphenhydramine (DPH) to prevent or minimize hypersensitivity reactions. The effects of NEXVIAZYME were evaluated based on comparison with a control group treated with DPH alone. Rabbits tested in reproductive toxicity studies were not pretreated with DPH because hypersensitivity reactions were not observed.

Embryo-fetal toxicity studies performed in pregnant mice at doses of 0, 10, 20, or 50 mg/kg/day administered intravenously once daily on gestational days 6 through 15 resulted in an immunologic response, including an anaphylactoid response, in some dams at the highest dose of 50 mg/kg/day (17 times the human steady-state AUC at the recommended biweekly dose of 20 mg/kg for LOPD patients weighing ≥30 kg or 10 times the human steady-state AUC at the recommended biweekly dose of 40 mg/kg for LOPD patients weighing <30 kg). Increased post-implantation loss and mean number of late resorptions were observed in this group. Placental transfer studies determined that avalglucosidase alfa-ngpt was not transported from the maternal to the fetal circulation in mice, suggesting that the embryo-fetal effects were due to maternal toxicity relating to the immunologic response. The maternal no observed adverse effect level (NOAEL) was 50 mg/kg/day intravenously (17 times the human AUC) and the developmental NOAEL was 20 mg/kg/day intravenously (4.8 times the human AUC).

Embryo-fetal toxicity studies performed in rabbits at doses of 0, 30, 60, and 100 mg/kg/day administered intravenously once daily on gestational days 6 through 19 resulted in no adverse effects in the fetuses at the highest dose (100 mg/kg/day; 91 times the human steady-state AUC at the recommended biweekly dosage of 20 mg/kg for LOPD patients weighing ≥30 kg or 50 times the human steady-state AUC at the recommended biweekly dose of 40 mg/kg for LOPD patients weighing <30 kg). Furthermore, the administration of NEXVIAZYME intravenously every other day in mice from gestational day 6 through postpartum day 20 did not produce adverse effects in the offspring at the highest dose of 50 mg/kg (maternal exposure not evaluated).

8.2 Lactation

Risk Summary

There are no data on the presence of avalglucosidase alfa-ngpt in either human or animal milk, the effects on the breastfed infant, or the effects on milk production. Available published literature suggests the presence of alglucosidase alfa (another hydrolytic lysosomal glycogen-specific enzyme replacement therapy) in human milk. The developmental and health benefits of breastfeeding should be considered along with the mother's clinical need for NEXVIAZYME and any potential adverse effects on the breastfed infant from NEXVIAZYME or from the underlying maternal condition.

Lactating women exposed to NEXVIAZYME, or their healthcare providers, should report NEXVIAZYME exposure by calling 1-800-633-1610, option 1.

8.4 Pediatric Use

The safety and effectiveness of NEXVIAZYME for the treatment of late-onset Pompe disease have been established in pediatric patients aged 1 year and older. Use of NEXVIAZYME for this indication is supported by evidence from two clinical studies which included adults with LOPD, and 1 pediatric patient with LOPD (16 years of age) and from safety experience in 19 pediatric patients with infantile-onset Pompe disease (IOPD) (1 to 12 years of age) treated with NEXVIAZYME [see Clinical Studies (14.1)]. NEXVIAZYME is not approved for the treatment of IOPD.

The safety profile of NEXVIAZYME in pediatric patients 1 to 12 years old with Pompe disease was similar to the safety profile of NEXVIAZYME in older pediatric and adult patients with LOPD. The safety and effectiveness of NEXVIAZYME have not been established in pediatric patients younger than 1 year of age.

8.5 Geriatric Use

Clinical studies with NEXVIAZYME included 13 patients 65 to 74 years of age and 4 patients 75 years of age and older. The recommended dosage in geriatric patients is the same as the recommended dosage in younger adult patients [see Adverse Reactions (6.1)].

11 DESCRIPTION

Avalglucosidase alfa-ngpt is a hydrolytic lysosomal glycogen-specific recombinant human α-glucosidase enzyme conjugated with multiple synthetic bis-mannose-6-phosphate (bis-M6P)-tetra-mannose glycans resulting in approximately 15 moles of M6P per mole of enzyme (15 M6P) and is produced in Chinese hamster ovary cells (CHO). Avalglucosidase alfa-ngpt has a molecular weight of approximately 124 kDa.

NEXVIAZYME (avalglucosidase alfa-ngpt) for injection is a sterile white to pale-yellow lyophilized powder for intravenous use after reconstitution and dilution. Each single-dose vial contains 100 mg of avalglucosidase alfa-ngpt, glycine (200 mg), L-Histidine (10.7 mg), L-Histidine HCl monohydrate (6.5 mg), mannitol (200 mg), and polysorbate 80 (1 mg). After reconstitution with 10 mL of Sterile Water for Injection, USP, the resultant concentration is 100 mg/10 mL (10 mg/mL) with a pH of approximately 6.2.

12 CLINICAL PHARMACOLOGY

12.1 Mechanism of Action

Pompe disease (also known as glycogen storage disease type II, acid maltase deficiency, and glycogenosis type II) is an inherited disorder of glycogen metabolism caused by a deficiency of the lysosomal enzyme acid α-glucosidase (GAA) that degrades glycogen to glucose in the lysosome. GAA deficiency results in intralysosomal accumulation of glycogen in various tissues.

Avalglucosidase alfa-ngpt provides an exogenous source of GAA. The M6P on avalglucosidase alfa-ngpt mediates binding to M6P receptors on the cell surface with high affinity. After binding, it is internalized and transported into lysosomes where it undergoes proteolytic cleavage that results in increased GAA enzymatic activity. Avalglucosidase alfa-ngpt then exerts enzymatic activity in cleaving glycogen.

12.2 Pharmacodynamics

In patients with Pompe disease, excess of glycogen is degraded to hexose tetrasaccharide (Hex4) which is then excreted in urine. The urinary Hex4 assay measures the major component, glucose tetrasaccharide (Glc4). Treatment with NEXVIAZYME resulted in reductions of urinary Glc4 concentrations (normalized by urine creatinine and reported as mmol Glc4/mol creatinine) in patients with Pompe disease.

In ERT-naïve LOPD patients in Study 1, the baseline mean (SD) urinary Glc4 concentration was 12.7 mmol/mol (10.10) and 8.7 mmol/mol (5.04) in NEXVIAZYME and alglucosidase alfa treatment groups, respectively [see Clinical Studies (14.1)]. At Week 145, the mean urinary Glc4 concentration was 4.32 mmol/mol (4.28) in patients who continued with NEXVIAZYME and 5.25 mmol/mol (7.48) in patients who switched from alglucosidase alfa to NEXVIAZYME.

For patients who started on NEXVIAZYME, the mean percentage (SD) change in urinary Glc4 concentration from baseline was -54% (24), at Week 49 and -53% (73) at Week 145. For patients who started on alglucosidase alfa and switched to NEXVIAZYME at Week 49, the mean percentage (SD) change in urinary Glc4 concentration from baseline was -11% (32) at Week 49, and -48% (42) at Week 145.

12.3 Pharmacokinetics

The avalglucosidase alfa-ngpt exposure increases in an approximately proportional manner with increasing doses over a range from 5 to 20 mg/kg (0.25 to 1 time the approved recommended dosage in LOPD patients weighing greater than or equal to 30 kg or 0.125 to 0.5 times the approved recommended dosage in LOPD patients weighing less than 30 kg). No accumulation was observed following every two weeks dosing. Following intravenous infusion of 20 mg/kg of NEXVIAZYME every two weeks in LOPD patients weighing greater than or equal to 30 kg, the mean ± SD plasma Cmax of avalglucosidase alfa-ngpt at Week 1 and Week 49 was 259 ± 72 µg/mL and 242 ± 81 µg/mL, respectively; the mean ± SD plasma AUC of avalglucosidase alfa-ngpt at Week 1 and Week 49 was 1,290 ± 420 µg∙h/mL and 1,250 ± 433 µg∙h/mL, respectively. Patients weighing less than 30 kg are expected to have similar AUC following intravenous infusion of 40 mg/kg of NEXVIAZYME every two weeks.

Distribution

The volume of distribution of avalglucosidase alfa-ngpt was 3.4 L in LOPD patients.

Elimination

The mean total body clearance of avalglucosidase alfa-ngpt was 0.9 L/hour and the mean plasma elimination half-life of avalglucosidase alfa-ngpt was 1.6 hours in LOPD patients.

Metabolism

The protein portion of avalglucosidase alfa-ngpt is expected to be metabolized into small peptides by catabolic pathways.

Specific Populations

Population pharmacokinetic analyses indicated that age, which ranged from 1 to 78 years in the clinical trials, and sex did not significantly influence the pharmacokinetics of avalglucosidase alfa-ngpt in patients with Pompe disease.

Pediatric patients

In 16 patients aged 1 to 12 years with Pompe disease, following a 4-hour intravenous infusion of NEXVIAZYME 20 mg/kg every two weeks and 7-hour intravenous infusion of NEXVIAZYME 40 mg/kg every two weeks, the mean Cmax ranged from 175 to 189 µg/mL and 250 to 403 µg/mL, respectively. The mean AUClast ranged from 805 to 923 µg∙hr/mL for 20 mg/kg every two weeks and 1,720 to 2,630 µg∙hr/mL for 40 mg/kg every two weeks.

12.6 Immunogenicity

The observed incidence of anti-drug antibodies (ADA) is highly dependent on the sensitivity and specificity of the assay. Differences in assay methods preclude meaningful comparisons of the incidence of ADAs in the studies described below with the incidence of ADAs in other studies, including those of NEXVIAZYME or of other avalglucosidase alfa products.

Table 5 presents the incidence of anti-avalglucosidase alfa-ngpt antibodies (referred to as ADA) in NEXVIAZYME-treated patients with Pompe disease [see Clinical Studies (14.1)]. In ERT-naïve LOPD patients who received NEXVIAZYME 20 mg/kg every two weeks for up to 436.2 weeks (with mean of 204.7 weeks), 95% (59/62) of patients developed ADA. The median time to seroconversion was 8 weeks.

ADA cross-reactivity studies showed that antibodies to avalglucosidase alfa-ngpt were cross-reactive to alglucosidase alfa.

Anti-Drug Antibody Effects on Pharmacokinetics

In Study 1, the avalglucosidase alfa-ngpt exposure (e.g., AUC) in the two ADA-negative NEXVIAZYME-treated patients was within the range of patients who developed ADA. Among the patients who developed ADA, the median AUC was similar between Week 1 and Week 49 irrespective of titer values and neutralizing activities of the ADA. There was no identified clinically significant effect of ADA on pharmacokinetics. [see Clinical Pharmacology (12.3)].

Anti-Drug Antibody Effects on Pharmacodynamics

In Study 1, a trend toward decreased pharmacodynamic response as measured by percent change of urinary glucose tetrasaccharides from baseline was observed in NEXVIAZYME-treated patients with an ADA peak titer ≥12,800 compared to those with a lower ADA peak titer.

Anti-Drug Antibody Effects on Safety and Efficacy

Increased incidence of IARs was observed in NEXVIAZYME-treated patients with higher ADA peak titers (>12,800) compared to those with lower ADA peaks. The incidence of hypersensitivity reactions was higher in ERT-experienced adult patients who developed ADA compared to those who were ADA-negative [see Adverse Reactions (6.1)]. In ERT-naïve patients, hypersensitivity reactions occurred irrespective of ADA development and peak ADA titer. In Study 1, there was no identified clinically significant effect of ADA on efficacy.

Table 5: Incidence of Anti-Avalglucosidase Alfa-ngpt Antibodies in NEXVIAZYME-treated Patients with Pompe Disease up to 100 months
 | ERT-Naïve Patients | ERT-Experienced Patients
 | Adult and Pediatric Patients [Includes two pediatric patients] 20 mg/kg every two weeks (N=62) [ERT-naïve: patients only treated with NEXVIAZYME] | Adults 20 mg/kg every two weeks (N=58) | Pediatric Patients 20 mg/kg every two weeks (N=6) | Pediatric Patients 40 mg/kg every two weeks (N=16)
 | n (%) | n (%) | n (%) | n (%)
ADA at baseline | 2 (3%) | 43 (74%) | 1 (17%) | 2 (13%)
ADA after NEXVIAZYME treatment | 59 (95%) | 36 (62%) | 1 (17%) | 9 (56%)
Neutralizing Antibody (NAb) After NEXVIAZYME Treatment
Both NAb types | 14 (23%) | 5 (9%) | 0 | 0
Inhibition of enzyme activity | 19 (31%) | 11 (19%) | 0 | 0
Inhibition of enzyme cellular uptake | 26 (42%) | 20 (34%) | 0 | 2 (13%)
‡ ERT-experienced: patients previously treated with alglucosidase alfa within a range of 0.9-9.9 years for adult patients and 0.6-11.8 years for pediatric patients before they received NEXVIAZYME.

13 NONCLINICAL TOXICOLOGY

13.1 Carcinogenesis, Mutagenesis, Impairment of Fertility

Long-term studies in animals to evaluate the carcinogenic potential or studies to evaluate mutagenic potential have not been performed with avalglucosidase alfa-ngpt.

Intravenous administration of avalglucosidase alfa-ngpt every other day at doses up to 50 mg/kg (exposure not evaluated) had no adverse effects on fertility in male or female mice.

14 CLINICAL STUDIES

14.1 Clinical Trial in Patients with Late-Onset Pompe Disease

Study 1 (NCT02782741) was a randomized, double-blinded, multinational, multicenter trial comparing the efficacy and safety of NEXVIAZYME to alglucosidase alfa in treatment-naïve patients with LOPD. One hundred patients (51 in NEXVIAZYME and 49 in alglucosidase alfa) were randomized in a 1:1 ratio based on baseline forced vital capacity ([FVC] % predicted; <55% or ≥55%), sex, age (<18 years or ≥18 years), and country (Japan or not-Japan) to receive 20 mg/kg of NEXVIAZYME or alglucosidase alfa administered intravenously once every two weeks for 49 weeks. After 49 weeks, all randomized patients in Study 1 had the option to enter an open-label extension treatment period to receive NEXVIAZYME and continue treatment up to at least Week 145.

Demographic and Disease Characteristics

Of the 100 randomized patients, 52 were males, the baseline median age was 49 years old (range from 16 to 78), median baseline weight was 76.4 kg (range from 38 to 139 kg), median length of time since diagnosis was 6.9 months (range from 0.3 to 328.4 months), mean age at diagnosis was 46.4 years old (range from 11 to 78), mean FVC (% predicted) at baseline was 62.1% (range from 32 to 85%), and mean 6MWT at baseline was 388.9 meters (range from 118 to 630 meters). The racial groups for the patients consisted of 94 White (94%), 3 Black or African American (3%), and 3 Asian (3%). Fifteen patients were Hispanic/Latino (15%), 76 non-Hispanic/Latino (76%) and 9 were not reported. Five patients (all in the alglucosidase alfa arm) discontinued the study prior to Week 49: four due to adverse events (acute myocardial infarction, arthritis, dyspnea, and urticaria), and one due to withdrawal of consent. All 95 patients who did not discontinue the study prior to Week 49 entered the open-label period (51 from the NEXVIAZYME arm and 44 from the alglucosidase alfa arm). Of the 95 patients, 77 patients had follow-up data on FVC (% predicted) at Week 145 (44 from the NEXVIAZYME arm and 33 from the alglucosidase alfa arm) and 80 patients had follow-up data on 6MWT at Week 145 (45 from the NEXVIAZYME arm and 35 from the alglucosidase alfa arm). Fourteen (14%) patients (7 in each group) discontinued during the Extension Treatment period (5 for adverse event, 1 for poor compliance to protocol and 8 for other reason).

Primary Efficacy Results from the 49-Week Active-Controlled Period and Open-Label Period up to Week 145 in Study 1

The primary endpoint of Study 1 was the change in FVC (% predicted) in the upright position from baseline to Week 49. At Week 49, the least squares (LS) mean change in FVC (% predicted) for patients treated with NEXVIAZYME and alglucosidase alfa was 2.9% and 0.5%, respectively. The estimated treatment difference was 2.4% (95% CI: -0.1, 5.0) favoring NEXVIAZYME (see Table 6). Figure 1 presents the LS mean change from baseline in FVC (% predicted) over time by treatment group up to Week 49.

Table 6: Summary Results of FVC (% predicted) in Upright Position in ERT-Naïve Patients with LOPD (Study 1) [All randomized patients]
 |  | NEXVIAZYME (n=51) | Alglucosidase Alfa (n=49)
Pretreatment baseline | Mean (SD) | 62.5 (14.4) | 61.6 (12.4)
Week 49 | Mean (SD) | 65.5 (17.4) | 61.2 (13.5)
Estimated change from baseline to week 49 | LS mean (SE) | 2.9 [Estimated using a mixed model for repeated measures (MMRM) including baseline FVC (% predicted, as continuous), sex, baseline age (years), treatment group, visit, and treatment-by-visit interaction term as fixed effects.] (0.9) | 0.5 (0.9)
Estimated difference between groups in change from baseline to week 49 | LS mean (95% CI) | 2.4 [Noninferiority margin of 1.1% (p=0.0074). Statistical superiority of NEXVIAZYME over alglucosidase alfa was not achieved (p=0.06).] (-0.1, 5.0)

Figure 1: Plot of LS Mean (SE) Change from Baseline of FVC (% predicted) in Upright Position over Time in ERT-Naïve Patients with LOPD (Study 1) [All randomized patients]

For patients who continued to receive NEXVIAZYME after Week 49 the mean change from baseline to Week 145 in FVC (% predicted) was 1.7 (SD=8.6, 95% CI: -0.9, 4.2), and the mean change from Week 49 to Week 145 was -0.8 (SD=6.2, 95% CI: -2.7, 1.0). For patients who switched from alglucosidase alfa to NEXVIAZYME after Week 49 the mean change from baseline to Week 145 was 0.5 (SD=8.3, 95% CI: -2.3, 3.4), and the mean change in FVC (% predicted) from Week 49 to Week 145 was 0.8 (SD=6.9) (95% CI: -1.6, 3.1).

Efficacy Results for Total Distance Walked in 6 Minutes from the 49-Week Active-Controlled Period and Open-Label Period up to Week 145 in Study 1

The key secondary endpoint of Study 1 was change in total distance walked in 6 minutes (6-Minute Walk Test, 6MWT) from baseline to Week 49. At Week 49, the LS mean change from baseline in 6MWT for patients treated with NEXVIAZYME and alglucosidase alfa was 32.2 meters and 2.2 meters, respectively. The estimated treatment difference was 30 meters (95% CI: 1.3, 58.7) favoring NEXVIAZYME (Table 7). Figure 2 presents the LS mean change from baseline in 6MWT distance over time by treatment group.

Table 7: Summary Results of 6-Minute Walk Test in ERT-Naïve Patients with LOPD (Study 1) [All randomized patients]
 |  | NEXVIAZYME (n=51) | Alglucosidase Alfa (n=49)
Pretreatment baseline | Mean (SD) | 399.3 (110.9) | 378.1 (116.2)
Week 49 | Mean (SD) | 441.3 (109.8) | 383.6 (141.1)
Estimated change from baseline to week 49 | LS mean (SE) | 32.2 [The MMRM model for 6MWT distance adjusts for baseline FVC (% predicted), baseline 6MWT (distance walked in meters), baseline age (years), sex, treatment group, visit, and treatment-by-visit interaction as fixed effects.] (9.9) | 2.2 (10.4)
Estimated difference between groups in change from baseline to week 49 | LS mean (95% CI) | 30.0 [p-value at nominal level, without multiplicity adjustment (p=0.04).] (1.3, 58.7)

Figure 2: Plot of LS Mean (SE) Change from Baseline of 6MWT (distance walked, in meters) over Time in ERT-Naïve Patients with LOPD (Study 1) [All randomized patients]

For patients who continued to receive NEXVIAZYME after Week 49 the mean change from baseline to Week 145 in 6MWT was 24.9 (SD=68.6, 95% CI: 4.8, 44.9), and the mean change from Week 49 to Week 145 was -11.0 (SD=33.5, 95% CI: -20.8, -1.2). For patients who switched from alglucosidase alfa to NEXVIAZYME after Week 49 the mean change from baseline to Week 145 in 6MWT was -4.1 (SD=90.4, 95% CI: -34.1, 25.8), and the mean change from Week 49 to Week 145 was -7.7 (SD=50.3, 95% CI: -24.4, 9.0).

16 HOW SUPPLIED/STORAGE AND HANDLING

How Supplied

NEXVIAZYME (avalglucosidase alfa-ngpt) for injection is supplied as a sterile, white to pale-yellow lyophilized powder in a single-dose vial. Each vial contains 100 mg of avalglucosidase alfa-ngpt. NEXVIAZYME is available as:

One single-dose vial in a carton (NDC 58468-0426-1)

Storage and Handling

Store refrigerated at 2°C to 8°C (36°F to 46°F). Do not use NEXVIAZYME after the expiration date on the vial.

17 PATIENT COUNSELING INFORMATION

Hypersensitivity Reactions Including Anaphylaxis and Infusion-Associated Reactions (IARs)

Advise the patient and caregiver that reactions related to the infusion may occur during and after NEXVIAZYME treatment, including life-threatening hypersensitivity reactions, including anaphylaxis, and IARs. Inform the patient and caregiver of the signs and symptoms of hypersensitivity reactions and IARs and to seek medical care should signs and symptoms occur [see Warnings and Precautions (5.1, 5.2)].

Risk of Acute Cardiorespiratory Failure

Advise the patient and caregiver that patients with underlying respiratory illness or compromised cardiac or respiratory function may be at risk of acute cardiorespiratory failure from volume overload during NEXVIAZYME infusion and should seek medical care should signs and symptoms occur [see Warnings and Precautions (5.3)].

NEXVIAZYME Exposure During Pregnancy or Lactation

Advise a pregnant or lactating woman exposed to NEXVIAZYME to report NEXVIAZYME exposure to her healthcare provider and by calling 1-800-633-1610, option 1 [see Use in Specific Populations (8.1., 8.2)].

Pompe Registry

Inform the patient and/or caregiver that there is a Pompe Registry to better understand the variability and progression of Pompe disease and to monitor and evaluate long-term effects of NEXVIAZYME. Encourage the patient and/or caregiver to enroll in the Pompe Registry and state that participation is voluntary and may involve long-term follow-up. For more information regarding the registry program, direct the patient and caregiver to visit www.registrynxt.com or call 1-800-745-4447, extension 15500.

Manufactured by:
Genzyme Corporation
Cambridge, MA 02141
A SANOFI COMPANY
U.S. License Number: 1596

This product's labeling may have been updated. For the most recent prescribing information, please visit www.nexviazyme.com.
©2023 Genzyme Corporation. All rights reserved.

PRINCIPAL DISPLAY PANEL - 100 mg Vial Carton

NDC 58468-0426-1
Rx only

Nexviazyme®
(avalglucosidase alfa-ngpt)
for Injection

100 mg per vial

For Intravenous Infusion
after Reconstitution
and Dilution

One single-dose vial
Discard unused portion